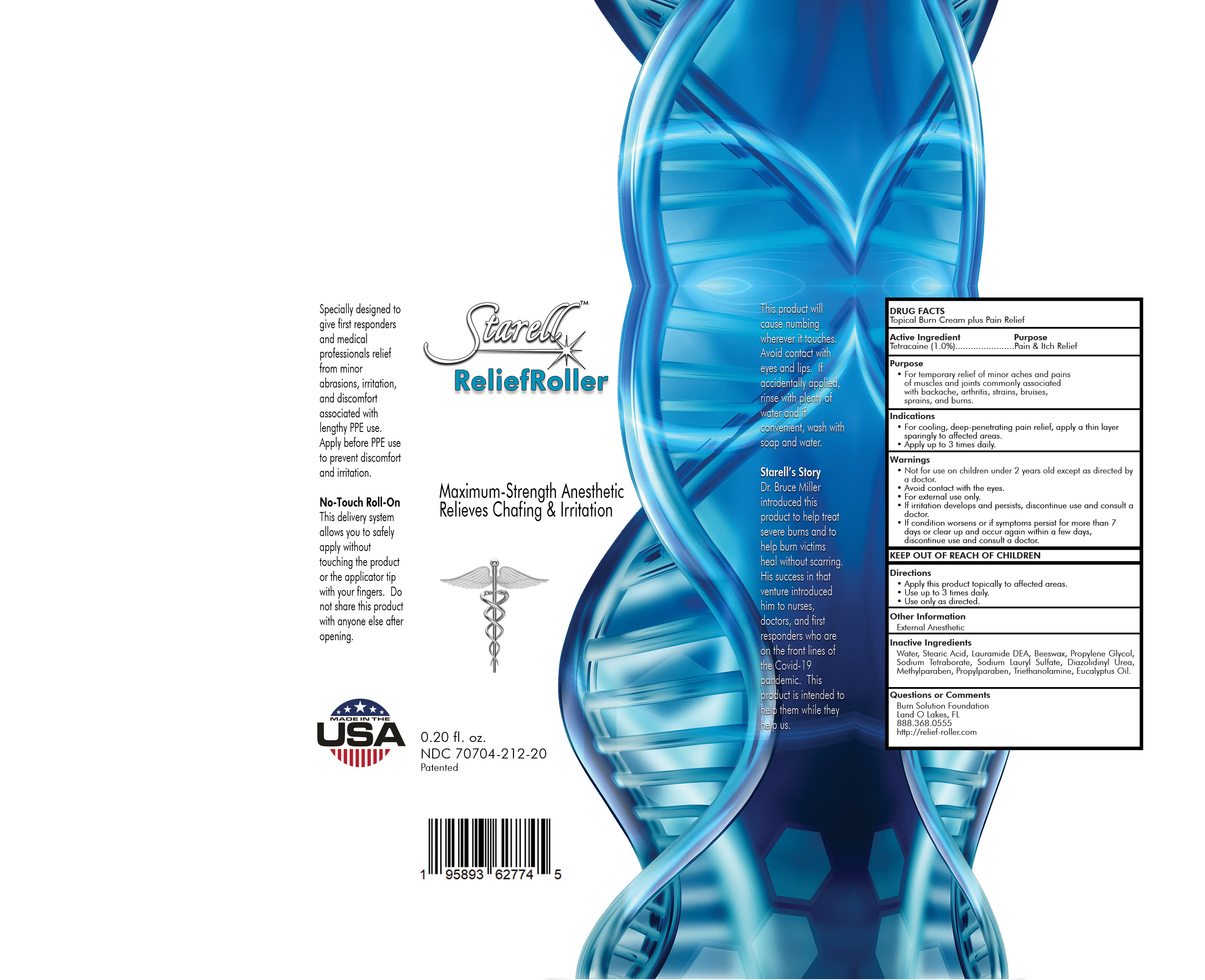 DRUG LABEL: burn solution cream
NDC: 70704-212 | Form: CREAM
Manufacturer: Burn Solution Foundations
Category: otc | Type: HUMAN OTC DRUG LABEL
Date: 20210426

ACTIVE INGREDIENTS: TETRACAINE 10 mg/1 mL
INACTIVE INGREDIENTS: METHYLPARABEN; PROPYLENE GLYCOL; TROLAMINE; DIAZOLIDINYL UREA; WATER; WHITE WAX; STEARIC ACID; SODIUM LAURYL SULFATE; SODIUM BORATE ANHYDROUS; LAURIC DIETHANOLAMIDE; EUCALYPTUS OIL; PROPYLPARABEN

Drug Facts

Topical Burn Cream plus Pain Relief

Active ingredient

Tetracaine (1.0%).......................Pain & Itch Relief

Purpose

For temporary relief of minor aches and pains of muscles and joints commonly associated with backache, arthritis, strains, bruises, sprains, and burns

Indications

• For cooling, deep-penetrating pain relief, apply a thin layer sparingly to affected areas.
• Apply up to 3 times daily

Warnings

• Not for use on children under 2 years old except as directed by a doctor.
• Avoid contact with the eyes.
• For external use only.
• If irritation develops and persists, discontinue use and consult a doctor.
• If condition worsens or if symptoms persist for more than 7 days or clear up and occur again within a few days, discontinue use and consult a doctor.

Directions

• Apply this product topically to affected areas.
• Use up to 3 times daily.
• Use only as directed.

Other Information

External Anesthetic

Inactive Ingredients

Water, Stearic Acid, Lauramide DEA, Beeswax, Propylene Glycol, Sodium Tetraborate, Sodium Lauryl Sulfate, Diazolidinyl Urea,
Methylparaben, Propylparaben, Triethanolamine, Eucalyptus Oil.

Questions or Comments

Burn Solution Foundation
Land O Lakes, FL
888.368.0555
http://relief-roller.com

PACKAGE LABEL

starell